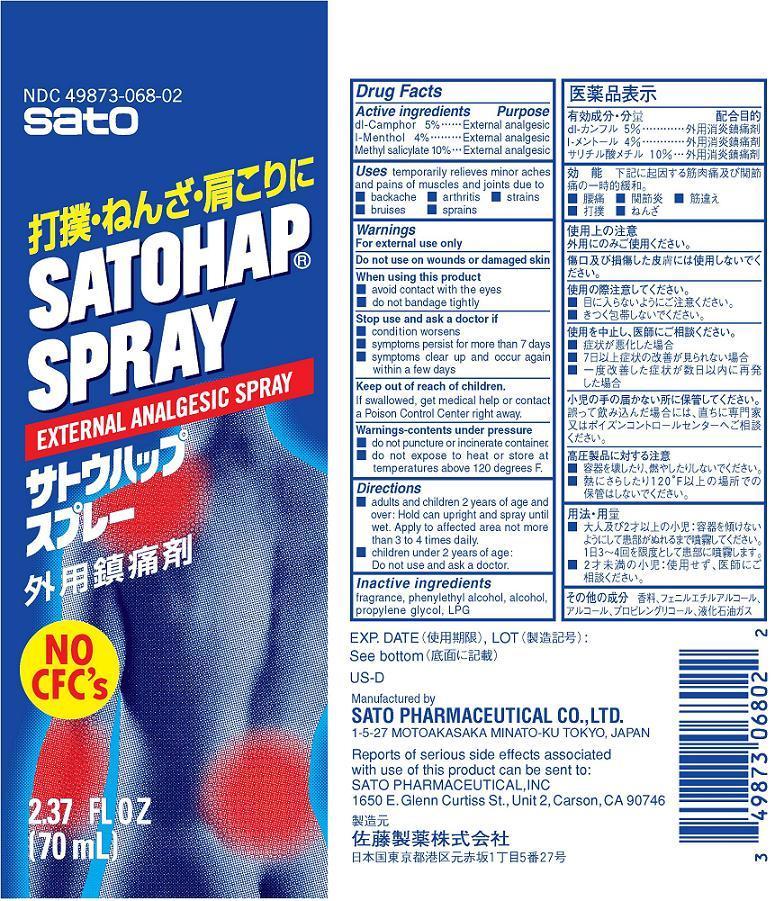 DRUG LABEL: Satohap
NDC: 49873-068 | Form: SPRAY
Manufacturer: Sato Pharmaceutical Co., Ltd.
Category: otc | Type: HUMAN OTC DRUG LABEL
Date: 20231128

ACTIVE INGREDIENTS: METHYL SALICYLATE 10 g/100 mL; LEVOMENTHOL 4 g/100 mL; CAMPHOR (SYNTHETIC) 5 g/100 mL
INACTIVE INGREDIENTS: PHENYLETHYL ALCOHOL; ALCOHOL; LIQUEFIED PETROLEUM GAS; PROPYLENE GLYCOL

Satohap Spray

Active ingredients
dl-Camphor 5%
l-Menthol 4%
Methyl salicylate 10%

Purpose
dl-Camphor External analgesic
l-Menthol External analgesic
Methyl salicylate External analgesic

INDICATIONS AND USAGE

Uses temporary relieves minor aches and pains of muscles and joints due to
■ backache ■ arthritis ■ strains ■ bruises ■sprains

Warnings

For external use only

Do not use on wounds or on damaged skin

When using this product
■ avoid contact with the eyes
■ do not bandage tightly

Stop use and ask a doctor if
■ symptoms persist for more than 7 days
■ symptoms clear up and occur again within a few days

Keep out of reach of children.
If swallowed, get medical help or contact a Poison Control Center right away.

SAFE HANDLING WARNING

Warnings-contents under pressure
■ do not puncture or incinerate container.
■ do not expose to heat or store at temperatures above 120 degrees F.

Directions
■ adults and children 2 years of age and over: Hold can upright and spray until wet. Apply to affected area not more than 3 to 4 times daily.
■ children under 2 years of age: Do not use and ask a doctor.

Inactive ingredients
fragrance, phenylethyl alcohol, alcohol, propylene glycol, LPG